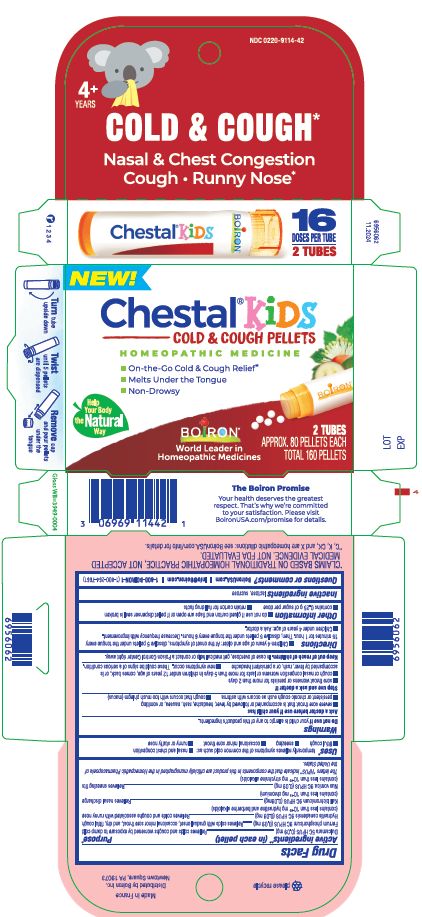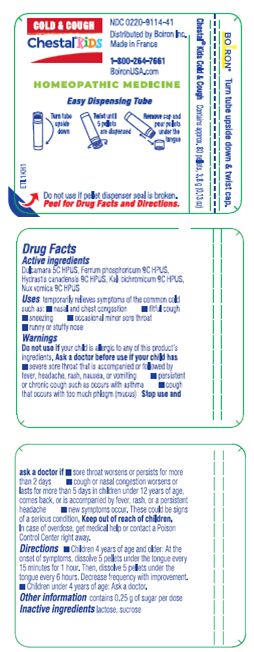 DRUG LABEL: Chestal Kids Cold and Cough
NDC: 0220-9114 | Form: PELLET
Manufacturer: Boiron
Category: homeopathic | Type: HUMAN OTC DRUG LABEL
Date: 20250117

ACTIVE INGREDIENTS: STRYCHNOS NUX-VOMICA SEED 9 [hp_C]/1 1; GOLDENSEAL 9 [hp_C]/1 1; POTASSIUM DICHROMATE 9 [hp_C]/1 1; FERROSOFERRIC PHOSPHATE 9 [hp_C]/1 1; SOLANUM DULCAMARA TOP 5 [hp_C]/1 1
INACTIVE INGREDIENTS: LACTOSE; SUCROSE

Chestal Kids Cold & Cough Pellets

Active ingredients**

Dulcamara 5C HPUS (0.09 mg)

Ferrum phosphoricum 9C HPUS (0.09 mg)

Hydrastis canadensis 9C HPUS (0.09 mg) (contains less than 10^-20 mg hydrastine and berberine alkaloids)

Kali bichromicum 9C HPUS (0.09 mg) (contains less than 10^-19 mg chromium)

Nux Vomica 9C HPUS (0.09 mg) (contains less than 10^-20 mg strychnine alkaloids)

The letters "HPUS" indicate that the components in this product are officially monographed in the Homeopathic Pharmacopoeia of the United States.

Purpose*

Dulcamara 5C HPUS (0.09 mg) ... Relieves cold and coughs worsened by exposure to damp cold

Ferrum phosphoricum 9C HPUS (0.09 mg) ... Relieves colds with gradual onset, occasional minor sore throat, and dry, fitful cough

Hydrastis canadensis 9C HPUS (0.09 mg) ... Relieves colds and coughs associated with runny nose

Kali bichromicum 9C HPUS (0.09 mg) (contains less than 10-19 mg chromium) ... Relieves nasal discharge

Nux Vomica 9C HPUS (0.09 mg) (contains less than 10-20 mg strychnine alkaloids) ... Relieves sneezing fits

Uses*

temporarily relieves symptoms of the common cold such as:

- nasal and chest congestion
- fitful cough
- sneezing
- occasional minor sore throat
- runny or stuff nose

Do not use if your child is allergic to any of this product's ingredients.

Ask a doctor before use if your child has

- severe sore throat that is accompanied or followed by fever, headache, rash, nausea, or vomiting
- persistent or chronic cough such as occurs with asthma
- cough that occurs with too much phlegm (mucus)

Stop use and ask a doctor if

- sore throat worsens or persists for more than 2 days
- cough or nasal congestion worsens or lasts for more than 5 days in children under 12 years of age, comes back, or is accompanied by fever, rash, or a persistent headache
- new symptoms occur. These could be signs of a serious condition.

PREGNANCY OR BREAST FEEDING

If pregnant or breast-feeding, ask a health professional before use.

Keep out of reach of children. In case of overdose, get medical help or contact a Poison Control Center right away.

DOSAGE AND ADMINISTRATION

- Children 4 years of age and older: At the onset of symptoms, dissolve 5 pellets under the tongue every 15 minutes for 1 hour. Then, dissolve 5 pellets under the tongue every 6 hours. Decrease frequency with improvement.
- Children under 4 years of age: Ask a doctor.

INACTIVE INGREDIENT

lactose, sucrose

QUESTIONS

BoironUSA.com

Info@Boiron.com

1-800-BOIRON-1

(1-800-264-7661)

Made in France

Distributed by Boiron, Inc.

Newtown Square, PA 19073

- do not use if glued carton end flaps are open or if pellet dispenser seal is broken
- contains 0.25 g of sugar per dose
- retain carton for full drug facts

Turn tube upside down

Twist until 5 pellets are dispensed

Remove cap and pour pellets under the tongue

COLD & COUGH*

Nasal & Chest Congestion Cough Runny Nose*

- On-the-Go Cold & Cough Relief*
- Melts Under the Tongue
- Non-Drowsy

2 TUBES

APPROX. 80 PELLETS EACH

TOTAL 160 PELLETS

*CLAIMS BASED ON TRADITIONAL HOMEOPATHIC PRACTICE NOT ACCEPTED MEDICAL EVIDENCE. NOT FDA EVALUATED.
**C,K,CK, and X are homeopathic dilutions: see BoironUSA.com/info for details.